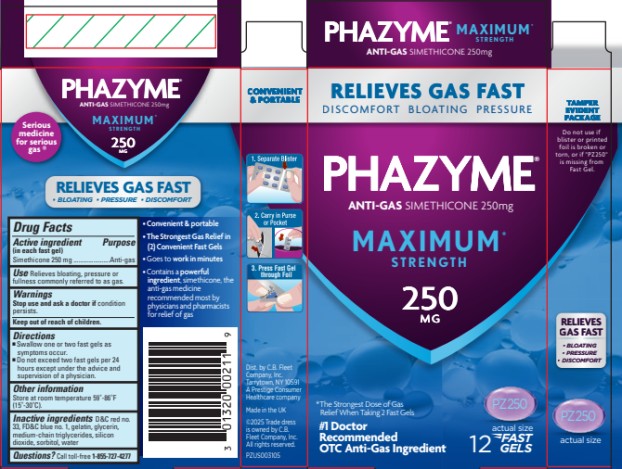 DRUG LABEL: PHAZYME
NDC: 0132-0211 | Form: CAPSULE, GELATIN COATED
Manufacturer: C.B. Fleet Company, Inc.
Category: otc | Type: HUMAN OTC DRUG LABEL
Date: 20251023

ACTIVE INGREDIENTS: DIMETHICONE 250 mg/1 1
INACTIVE INGREDIENTS: D&C RED NO. 33; FD&C BLUE NO. 1; GELATIN; GLYCERIN; MEDIUM-CHAIN TRIGLYCERIDES; SILICON DIOXIDE; SORBITOL; WATER

Phazyme Maximum Strength 250 mg 0132 - 0211

Drug Facts

Active Ingredient (in each fast gel)

Simethicone 250 mg

Purpose

Anti-gas

Use

Relieves bloating, pressure or fullness commonly referred to as gas

Warnings

Stop use and ask a doctor if

condition persists.

Directions

- Swallow one or two fast gels as symptoms occur.
- Do not exceed two fast gels per 24 hours except under the advice and supervision of a physician.

Other information

Store at room temperature 59º-86ºF (15º-30ºC).

Inactive Ingredients

DC Red #33, FD&C Blue #1, gelatin, glycerin, medium-chain triglycerides, silicon dioxide, sorbitol, purified water

Questions?

Call toll-free 1-855-727-4277

Principal Display Panel

PHAZYME®

ANTI-GAS SIMETHICONE 250 mg

MAXIMUM
STRENGTH

250 MG

12 FAST GELS